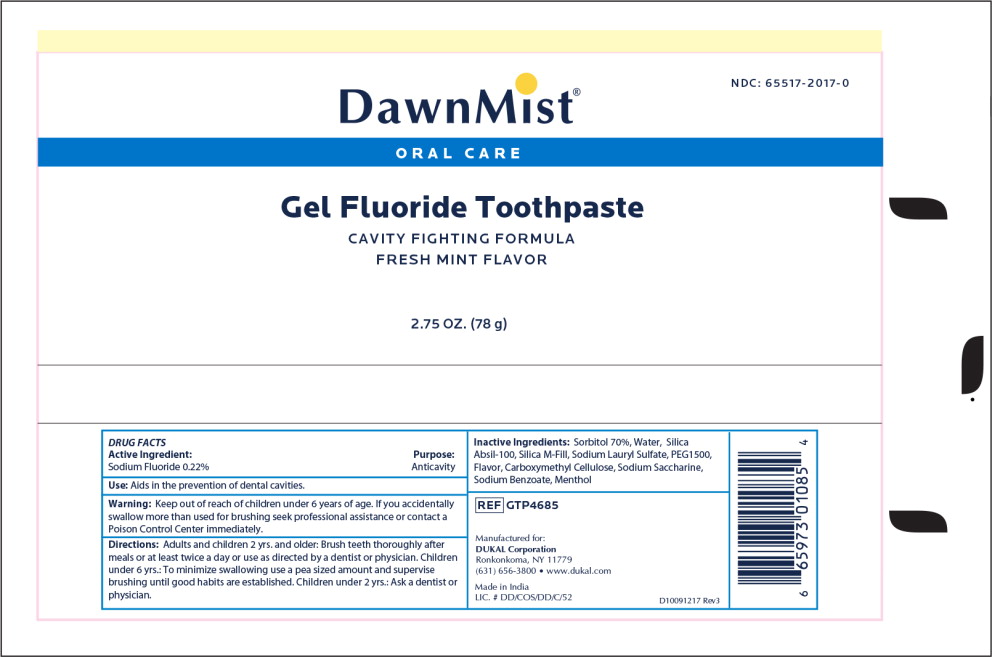 DRUG LABEL: DAWNMIST FLUORIDE
NDC: 65517-2017 | Form: PASTE
Manufacturer: Dukal LLC
Category: otc | Type: HUMAN OTC DRUG LABEL
Date: 20240708

ACTIVE INGREDIENTS: SODIUM FLUORIDE 0.22 g/100 g
INACTIVE INGREDIENTS: WATER; SORBITOL; SILICON DIOXIDE; SODIUM LAURYL SULFATE; POLYETHYLENE GLYCOL 1500; CARBOXYMETHYLCELLULOSE; SODIUM BENZOATE; SACCHARIN SODIUM

DawnMist Gel Fluoride Toothpaste

Active Ingredient

Sodium Fluoride 0.22%

Purpose

Anticavity

Use

Aids in the prevention of dental cavities

Keep out of reach of children under 6 years of age

If you accidently swallow more than used for brushing seek professional assistance or contact a Poison Control immediately

Directions

Adults and children 2 years and older: Brush teeth thoroughly after meals or at least twice a day or use as directed by a dentist or physician.

Children under 6 years: To minimize swallowing, use a peas sized amount and supervisor brushing until good habits are established.

Children under 2 years: Ask a dentist or physician

Inactive Ingredient

Sorbitol, Water, Silica, Sodium Lauryl Sulphate, PEG1500, Flavor, Carboxymethyl Cellulose, Sodium Benzoate, Sodium Saccharin

Principal Display Panel - DawnMist Gel Fluoride Toothpaste 2.75 oz Tube Label

DawnMist®

NDC: 65517-2017-0

ORAL CARE

Gel Fluoride Toothpaste

CAVITY FIGHTING FORMULA

FRESH MINT FLAVOR

2.75 OZ. (78 g)